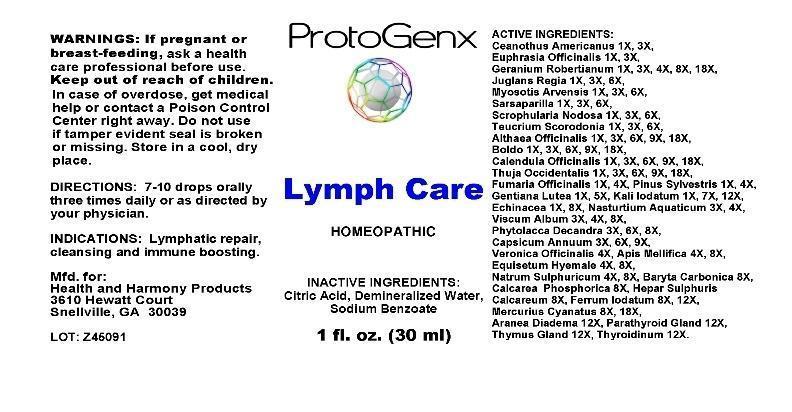 DRUG LABEL: Lymph Care
NDC: 51730-0002 | Form: LIQUID
Manufacturer: Health and Harmony Products
Category: homeopathic | Type: HUMAN OTC DRUG LABEL
Date: 20130814

ACTIVE INGREDIENTS: CEANOTHUS AMERICANUS LEAF 1 [hp_X]/1 mL; EUPHRASIA STRICTA 1 [hp_X]/1 mL; GERANIUM ROBERTIANUM 1 [hp_X]/1 mL; JUGLANS REGIA LEAF 1 [hp_X]/1 mL; JUGLANS REGIA FRUIT RIND, IMMATURE 1 [hp_X]/1 mL; MYOSOTIS ARVENSIS 1 [hp_X]/1 mL; SARSAPARILLA 1 [hp_X]/1 mL; SCROPHULARIA NODOSA 1 [hp_X]/1 mL; TEUCRIUM SCORODONIA FLOWERING TOP 1 [hp_X]/1 mL; ALTHAEA OFFICINALIS ROOT 1 [hp_X]/1 mL; PEUMUS BOLDUS LEAF 1 [hp_X]/1 mL; CALENDULA OFFICINALIS FLOWERING TOP 1 [hp_X]/1 mL; THUJA OCCIDENTALIS LEAF 1 [hp_X]/1 mL; FUMARIA OFFICINALIS FLOWERING TOP 1 [hp_X]/1 mL; PINUS SYLVESTRIS LEAFY TWIG 1 [hp_X]/1 mL; GENTIANA LUTEA ROOT 1 [hp_X]/1 mL; POTASSIUM IODIDE 1 [hp_X]/1 mL; ECHINACEA, UNSPECIFIED 1 [hp_X]/1 mL; NASTURTIUM OFFICINALE 3 [hp_X]/1 mL; VISCUM ALBUM FRUITING TOP 3 [hp_X]/1 mL; PHYTOLACCA AMERICANA ROOT 3 [hp_X]/1 mL; CAPSICUM 3 [hp_X]/1 mL; VERONICA OFFICINALIS FLOWERING TOP 4 [hp_X]/1 mL; APIS MELLIFERA 4 [hp_X]/1 mL; EQUISETUM HYEMALE 4 [hp_X]/1 mL; SODIUM SULFATE 4 [hp_X]/1 mL; BARIUM CARBONATE 8 [hp_X]/1 mL; TRIBASIC CALCIUM PHOSPHATE 8 [hp_X]/1 mL; CALCIUM SULFIDE 8 [hp_X]/1 mL; FERROUS IODIDE 8 [hp_X]/1 mL; MERCURIC CYANIDE 8 [hp_X]/1 mL; ARANEUS DIADEMATUS 12 [hp_X]/1 mL; BOS TAURUS PARATHYROID GLAND 12 [hp_X]/1 mL; BOS TAURUS THYMUS 12 [hp_X]/1 mL; SUS SCROFA THYROID 12 [hp_X]/1 mL
INACTIVE INGREDIENTS: CITRIC ACID MONOHYDRATE; WATER; SODIUM BENZOATE

DRUG FACTS:

ACTIVE INGREDIENTS:

Ceanothus Americanus 1X, 3X, Euphrasia Officinalis 1X, 3X, Geranium Robertianum 1X, 3X, 4X, 8X, 18X, Juglans Regia 1X, 3X, 6X, Myosotis Arensis 1X, 3X, 6X, Sarsaparilla 1X, 3X, 6X, Scrophularia Nodosa 1X, 3X, 6X, Teucrium Scorodonia 1X, 3X, 6X, Althaea Officinalis 1X, 3X, 6X, 9X, 18X, Boldo 1X, 3X, 6X, 9X, 18X, Calendula Officinalis 1X, 3X, 6X, 9X, 18X, Thuja Occidentalis 1X, 3X, 6X, 9X, 18X, Fumaria Officinalis 1X, 4X, Pinus Sylvestris 1X, 4X, Gentiana Lutea 1X, 5X, kali Iodatum 1X, 7X, 12X, Echinacea 1X, 8X, Nasturtium Aquaticum 3X, 4X, Viscum Album 3X, 4X, 8X, Phytolacca Decandra 3X, 6X, 8X, Capsicum Annuum 3X, 6X, 9X, Veronica Officinalis 4X, Apis Mellifica 4X, 8X, Equisetum Hyemale 4X, 8X, Natrum Sulphuricum 4X, 8X, Baryta Carbonica 8X, Calcarea Phosphorica 8X, Hepar Sulphuris Calcareum 8X, Ferrum Iodatum 8X, 12X, Mercurius Cyanatus 8X, 12X, Aranea Diadema 12X, Parathyroid Gland (Bovine) 12X, Thymus Gland (Bovine) 12X, Thyroidinum (Suis) 12X.

INDICATIONS:

Lymphatic repair, cleansing and immune boosting.

WARNINGS:

If pregnant or breast-feeding, ask a health care professional before use.

Keep out of reach of children. In case of overdose, get medical help or contact a Poison Control Center right away.

Do not use if tamper evident seal is broken or missing.

STORAGE:

Sore in a cool, dry place.

DIRECTIONS:

7-10 drops orally three times daily or as directed by your physician.

INACTIVE INGREDIENTS:

Citric Acid, Demineralized Water, Sodium Benzoate

Keep out of reach of children. In case of overdose, get medical help or contact a Poison Control Center right away.

INDICATIONS:

Lymphatic repair, cleansing and immune boosting.

QUESTIONS:

Mfd. for:

Health and Harmony Products

3610 Hewatt Court

Snellville, GA 30039

PACKAGE DISPLAY LABEL:

ProtoGenx

Lymph Care

HOMEOPATHIC

1 fl. oz. (30 mL)